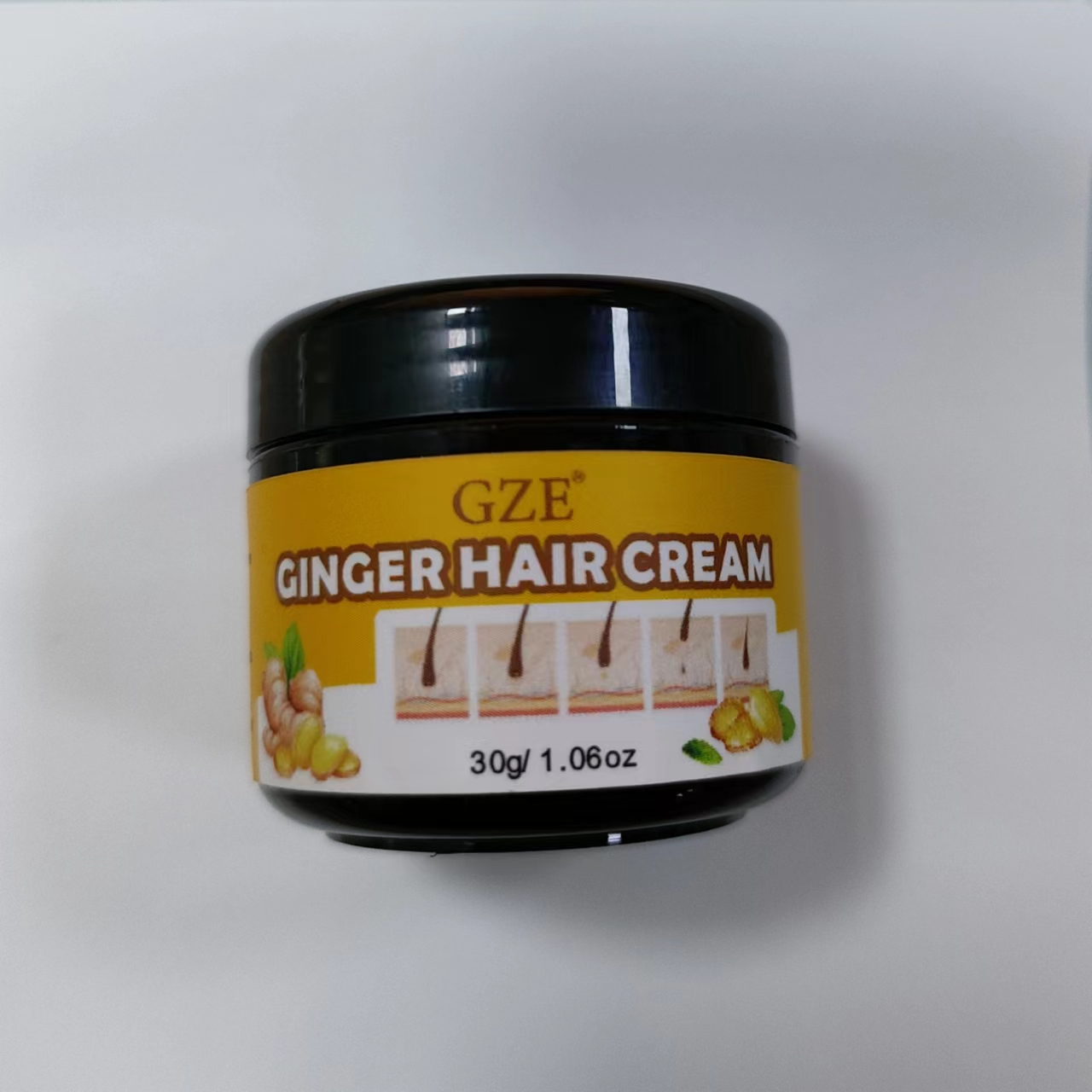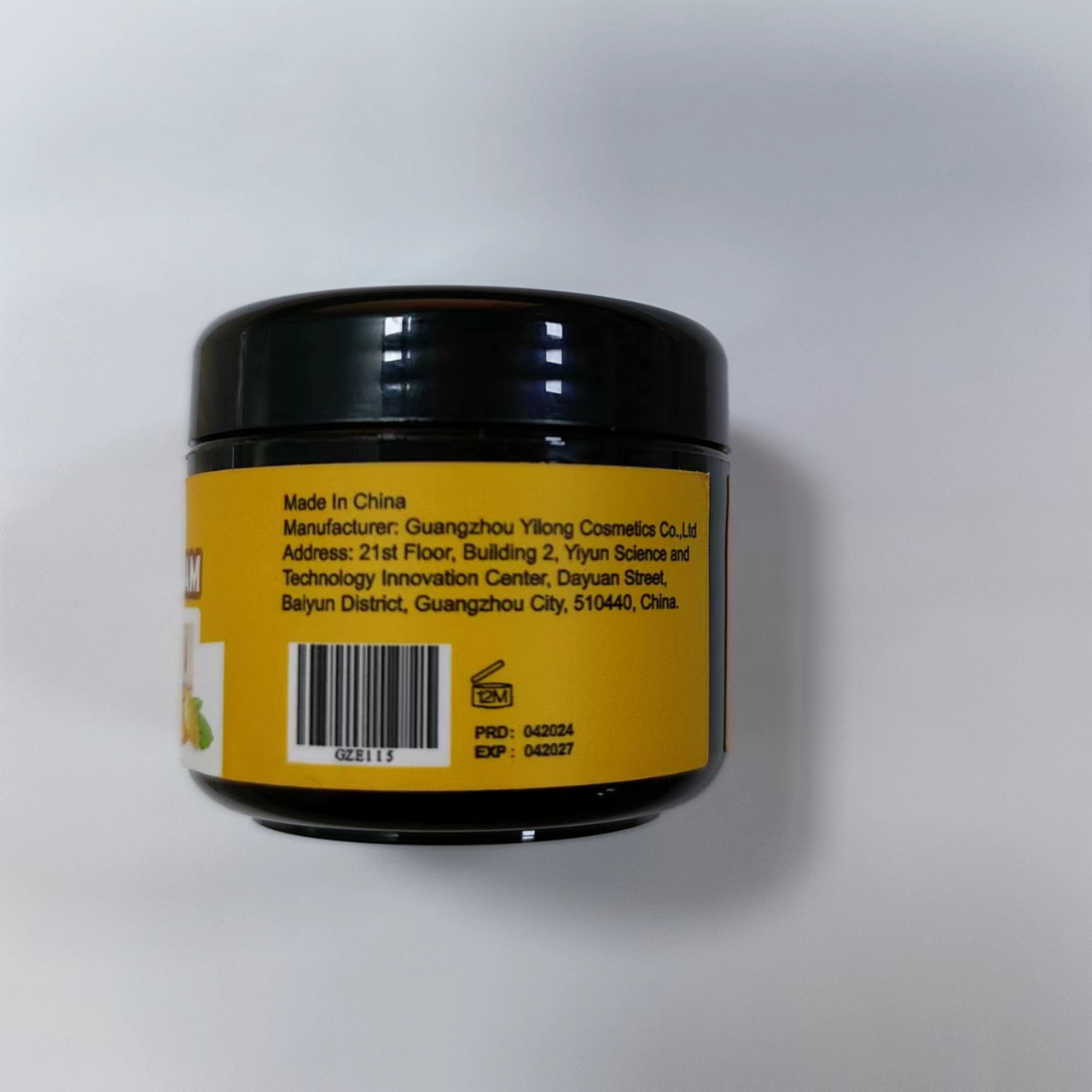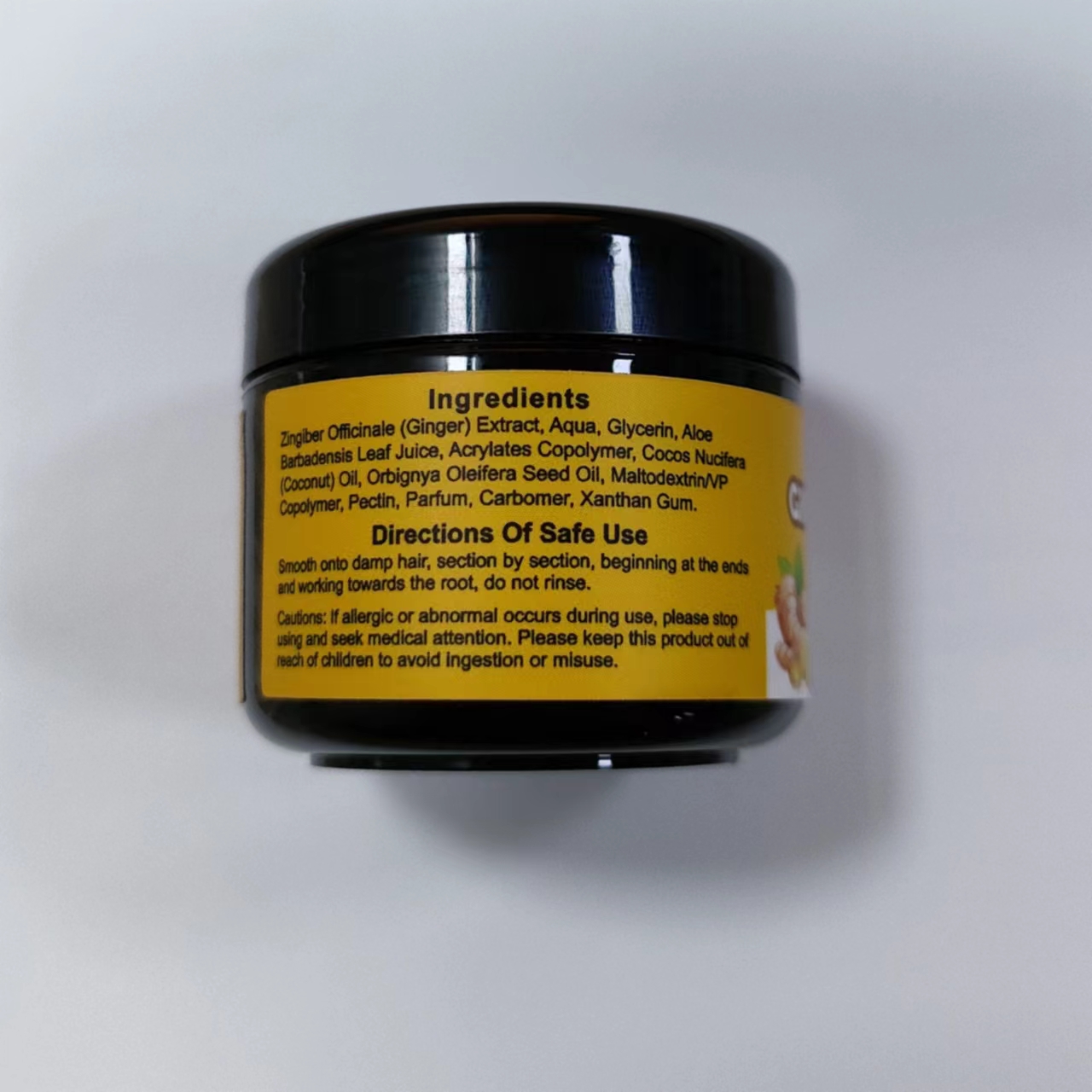 DRUG LABEL: GZE Ginger Hair Cream
NDC: 83566-115 | Form: CREAM
Manufacturer: Guangzhou Yilong Cosmetics Co., Ltd
Category: otc | Type: HUMAN OTC DRUG LABEL
Date: 20240610

ACTIVE INGREDIENTS: COCONUT OIL 2 mg/30 g; ZINGIBER OFFICINALE WHOLE 46.4 mg/30 g; ALOE VERA LEAF 10 mg/30 g; OLIVE OIL 2 mg/30 g
INACTIVE INGREDIENTS: PARFUMIDINE; GLYCERIN; PECTIN; WATER; CARBOMER 940; MALTODEXTRIN/VP COPOLYMER (1000 MPA.S); XANTHAN GUM; ACRYLATES CROSSPOLYMER-4

GZE Ginger Hair Cream

ACTIVE INGREDIENT

COCONUT OIL
ZINGIBER OFFICINALE WHOLE
OLIVE OIL
ALOE VERA LEAF

PURPOSE

Hair Care.

INDICATIONS AND USAGE

Smooth onto damp hair, section by section, beginning at the ends and working towards the root, do not rinse.

WARNINGS

For external use only.

Stop use and ask a doctor if rash occurs.

Do not use on damaged or broken skin.

When using this product keep out of eyes. Rinse with water to remove.

Keep out of reach of children. If swallowed, get medical help or contact a Poison Control Center right away.

DOSAGE AND ADMINISTRATION

Squeeze out an appropriate amount of ginger hair cream,smooth onto damp hair, section by section, beginning at the ends and working towards the root, do not rinse.

INACTIVE INGREDIENT

PARFUMIDINE
GLYCERIN
PECTIN
WATER
XANTHAN GUM
ACRYLATES CROSSPOLYMER-4
MALTODEXTRINNP COPOLYMER (1000 MPA.S)
CARBOMER 940